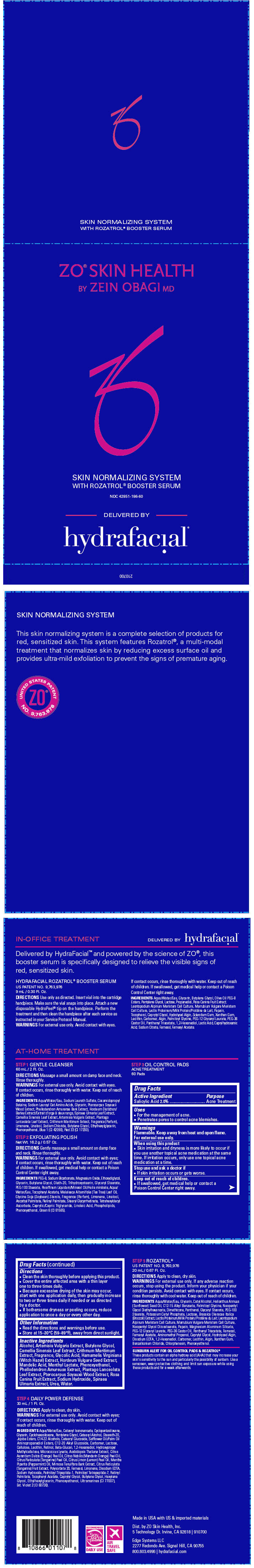 DRUG LABEL: ZO Skin Health Skin Normalizing System with Rozatrol Booster Serum
NDC: 42851-186 | Form: KIT | Route: TOPICAL
Manufacturer: ZO Skin Health, Inc.
Category: otc | Type: HUMAN OTC DRUG LABEL
Date: 20200420

ACTIVE INGREDIENTS: SALICYLIC ACID 20 mg/1 mL
INACTIVE INGREDIENTS: ALCOHOL; BUTYLENE GLYCOL; GREEN TEA LEAF; CRITHMUM MARITIMUM; GLYCOLIC ACID; HAMAMELIS VIRGINIANA TOP; BARLEY; MANDELIC ACID; MENTHYL LACTATE, (-)-; PHENOXYETHANOL; PLANTAGO LANCEOLATA LEAF; PTEROCARPUS SOYAUXII WOOD; ROSA CANINA FRUIT; SODIUM HYDROXIDE; UREA; WATER

ZO® Skin Health Skin Normalizing System with Rozatrol® Booster Serum

Drug Facts

Active Ingredient

Salicylic Acid 2.0%

Purpose

Acne Treatment

Uses

- For the management of acne.
- Penetrates pores to control acne blemishes.

Warnings

Flammable. Keep away from heat and open flame.

For external use only.

When using this product

- Skin irritation and dryness is more likely to occur if you use another topical acne medication at the same time. If irritation occurs, only use one topical acne medication at a time.

Stop use and ask a doctor if

- If skin irritation occurs or gets worse.

Keep out of reach of children.

- If swallowed, get medical help or contact a Poison Control Center right away.

Directions

- Clean the skin thoroughly before applying this product.
- Cover the entire affected area with a thin layer one to three times daily.
- Because excessive drying of the skin may occur, start with one application daily, then gradually increase to two or three times daily if needed or as directed by a doctor.
- If bothersome dryness or peeling occurs, reduce application to once a day or every other day.

Other Information

- Read the directions and warnings before use.
- Store at 15–30°C (59–89°F), away from direct sunlight.

Inactive Ingredients

Alcohol, Artemisia Vulgaris Extract, Butylene Glycol, Camellia Sinensis Leaf Extract, Crithmum Maritimum Extract, Fragrance, Glycolic Acid, Hamamelis Virginiana (Witch Hazel) Extract, Hordeum Vulgare Seed Extract, Mandelic Acid, Menthyl Lactate, Phenoxyethanol, Phellodendron Amureuse Extract, Plantago Lanceolata Leaf Extract, Pterocarpus Soyauxii Wood Extract, Rosa Canina Fruit Extract, Sodium Hydroxide, Spiraea Ulmaria Extract, Urea, Water.

Dist. by ZO Skin Health, Inc.
5 Technology Dr. Irvine, CA 92618 | 910700

PRINCIPAL DISPLAY PANEL - Kit Carton

ZO® SKIN HEALTH
BY ZEIN OBAGI MD

SKIN NORMALIZING SYSTEM
WITH ROZATROL® BOOSTER SERUM

NDC 42851-186-60

DELIVERED BY

hydrafacial©